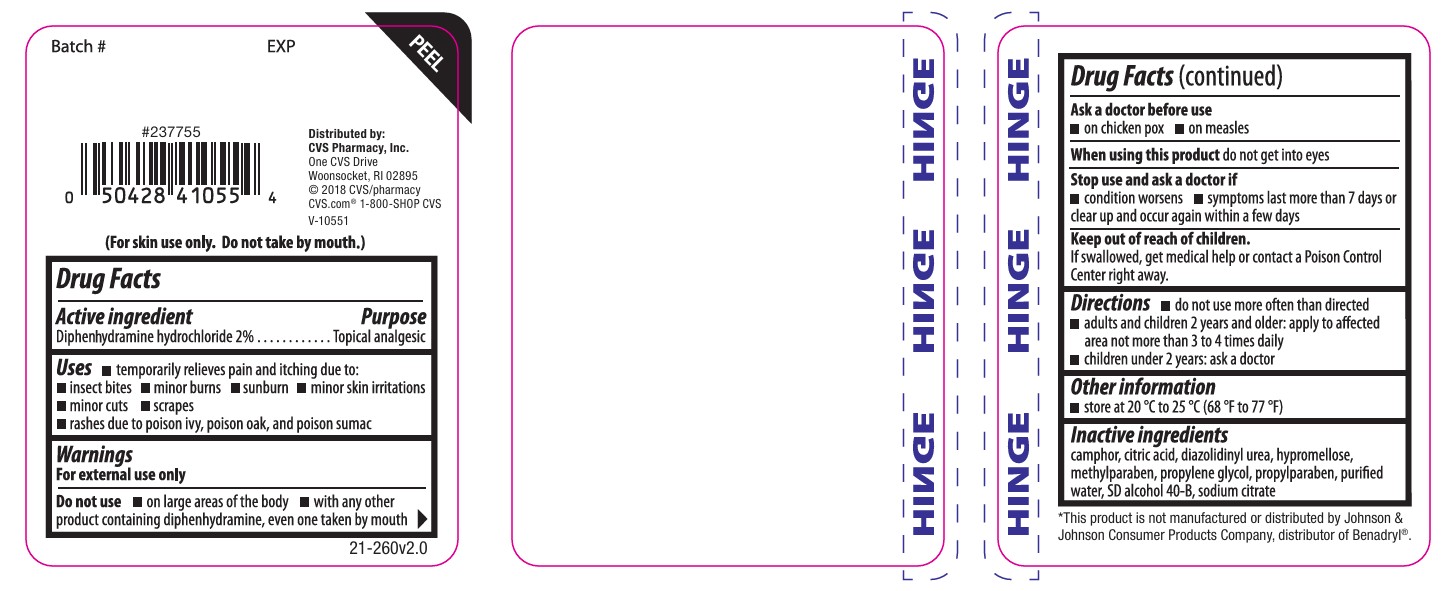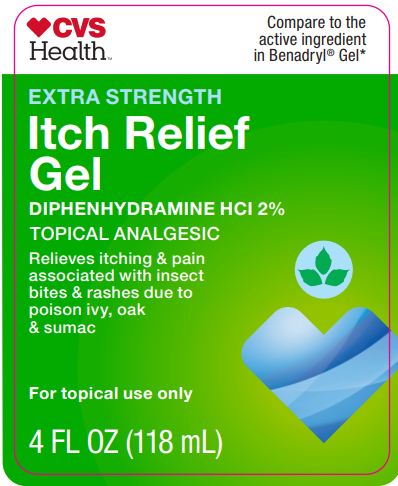 DRUG LABEL: Itch Stopping
NDC: 69842-620 | Form: GEL
Manufacturer: CVS
Category: otc | Type: HUMAN OTC DRUG LABEL
Date: 20251112

ACTIVE INGREDIENTS: DIPHENHYDRAMINE HYDROCHLORIDE 2 g/100 g
INACTIVE INGREDIENTS: TRISODIUM CITRATE DIHYDRATE; DIAZOLIDINYL UREA; METHYLPARABEN; PROPYLPARABEN; ALCOHOL; WATER; PROPYLENE GLYCOL; ANHYDROUS CITRIC ACID; HYPROMELLOSE 2910 (4000 MPA.S); CAMPHOR (SYNTHETIC)

CVS Extra Strength Itch Stopping Gel

ACTIVE INGREDIENT

Diphenhydramine hydrochloride 2%

INDICATIONS AND USAGE

temporary relieves pain and itching due to:

insect bites

minor burns

sunburn

minor skin irritations

minor cuts

scrapes

rashes due to poison ivy, poison oak, and poison sumac

WARNINGS

For external use only

DO NOT USE

on large areas of the body

with any other product containing diphenhydramine, even one taken by mouth

ASK DOCTOR/PHARMACIST

On chiken Pox

On Measles

WHEN USING

do not get into eyes

STOP USE

condition worsens

symptoms last more than 7 days or clear up and occur again within a few days

KEEP OUT OF REACH OF CHILDREN

If swallowed, get medical help or contact a Poison Control Center right away.

PURPOSE

Anti itch

Topical analgesic

STORAGE AND HANDLING

store at 20 °C to 25 °C (68 °F to 77 °F)

INACTIVE INGREDIENT

camphor, citric acid, diazolidinyl urea, hypromellose, methylparaben, propylene glycol, propylparaben, purified water,
SD alcohol 40-B, sodium citrate

do not use more often than directed

adults and children 2 years and older: apply to affected area not more than 3 to 4 times daily

children under 2 years: ask a doctor

RECENT MAJOR CHANGES

Dosage & Administration Section

Added- do not use more often than directed

PACKAGE LABEL

CVS health

Compare to the active ingredient in Benadryl Gel

Extra strength Itch Relief Gel

Diphenhydramine HCL 2%

Topical analgesic

Relives itching & pain associated with insect bites & rashes due to poison ivy, oak & sumac

For topical use only